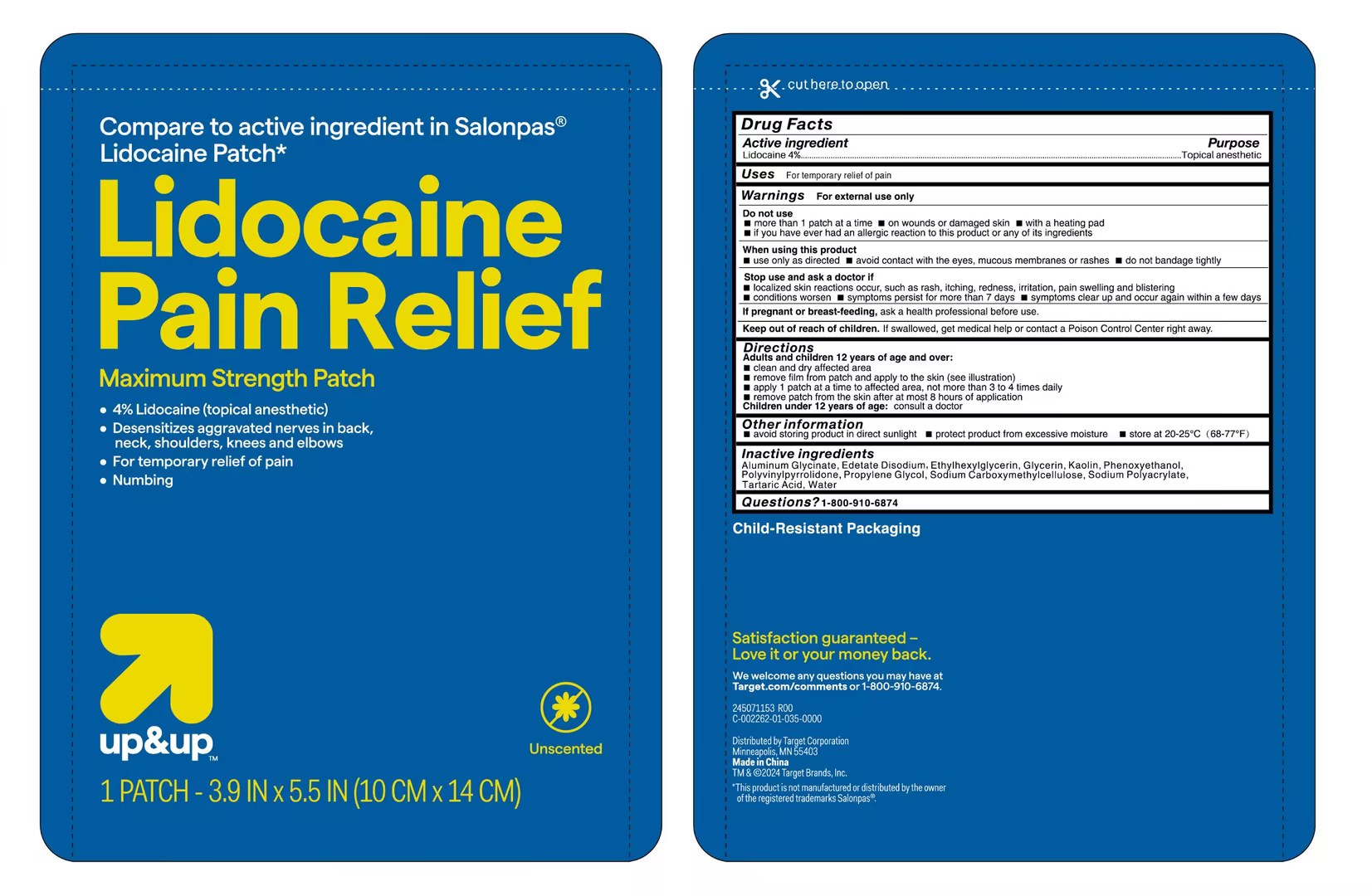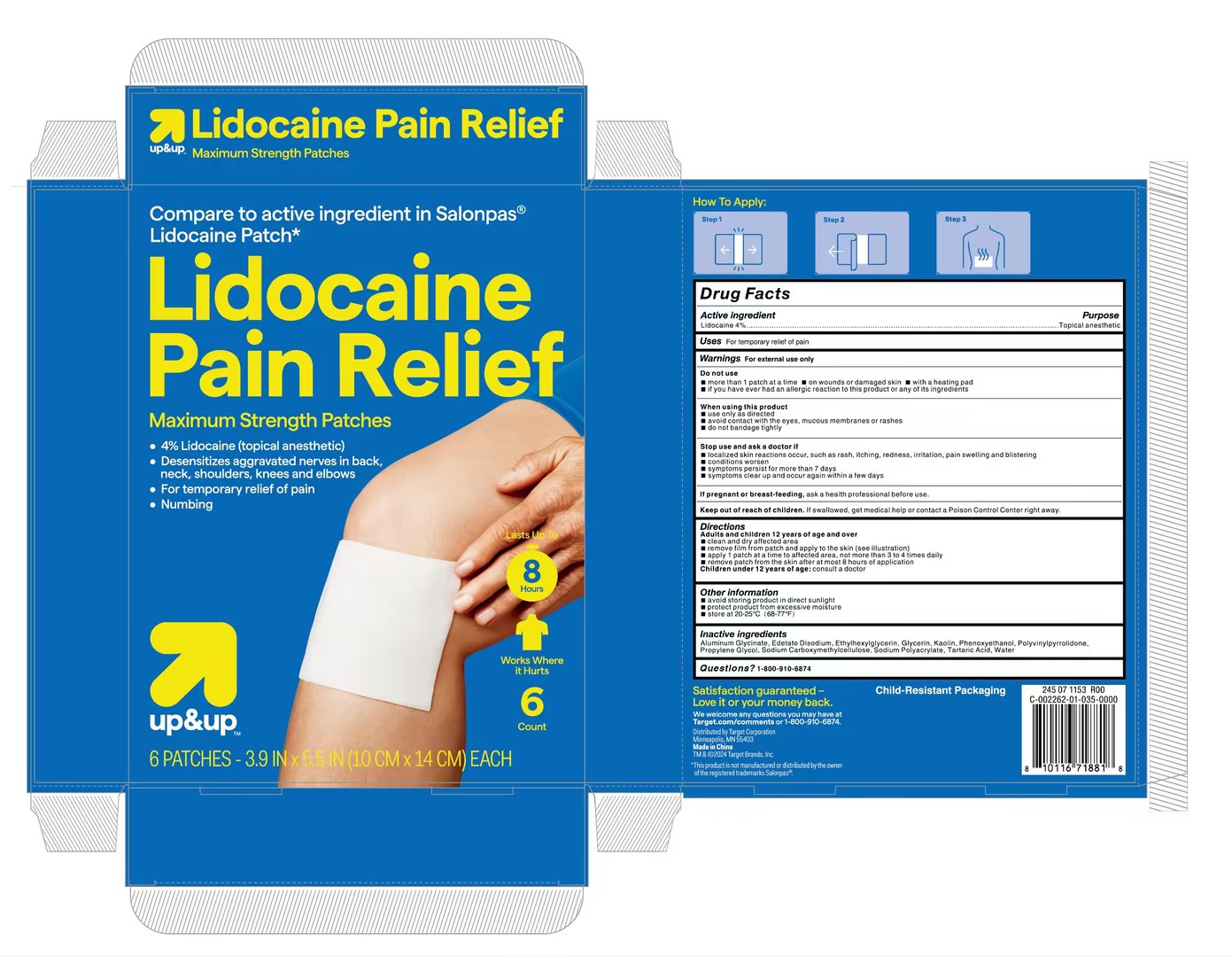 DRUG LABEL: Lidocaine Pain Relief Patch
NDC: 83559-004 | Form: PATCH
Manufacturer: Henan Enokon Medical Instrument Co., Ltd.
Category: otc | Type: HUMAN OTC DRUG LABEL
Date: 20240408

ACTIVE INGREDIENTS: LIDOCAINE 4 g/100 1
INACTIVE INGREDIENTS: EDETATE DISODIUM; TARTARIC ACID; ETHYLHEXYLGLYCERIN; CARBOXYMETHYLCELLULOSE SODIUM; DIHYDROXYALUMINUM AMINOACETATE ANHYDROUS; GLYCERIN; KAOLIN; PHENOXYETHANOL; POVIDONE; WATER; PROPYLENE GLYCOL; SODIUM ACRYLATE

83559-004

Active Ingredient

Lidocaine 4%

Purpose

Topical analgesic

Use

For temporary relief of pain

Warnings

For external use only

Do not use

more than 1 patch at a time
on wounds or damaged skin
with a heating pad
if you have ever had an allergic reaction to this product or any of its ingredients

When Using

use only as directed
avoid contact with the eyes, mucous membranes or rashes
do not bandage tightly

Stop Use

localized skin reactions occur, such as rash, itching, redness, irritation, pain swelling and blistering conditions worsen
symptoms persist for more than 7 days
symptoms clear up and occur again within a few days

Ask Doctor

If pregnant or breast-feeding, ask a health professional before use.
Children under 12 years of age: consult a doctor

Keep Out Of Reach Of Children

If swallowed, get medical help or contact a Poison Control Center right away.

Directions

Adults and children 12 years of age and over
clean and dry affected area
remove film from patch and apply to the skin (see illustration)
apply 1 patch at a time to affected area, not more than 3 to 4 times daily
remove patch from the skin after at most 8 hours of application
Children under 12 years of age: consult a doctor

Other information

avoid storing product in direct sunlight
protect product from excessive moisture
store at 20-25°C(68-77°F)

Inactive ingredients

Aluminum Glycinate, Edetate Disodium, Ethylhexylglycerin, Glycerin, Kaolin, Phenoxyethanol, Polyvinylpyrrolidone, Propylene Glycol, Sodium Carboxymethylcellulose, Sodium Polyacrylate, Tartaric Acid, Water

Questions

1-800-910-6874